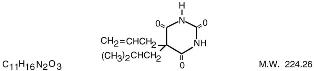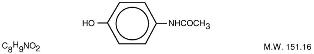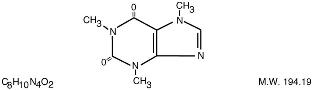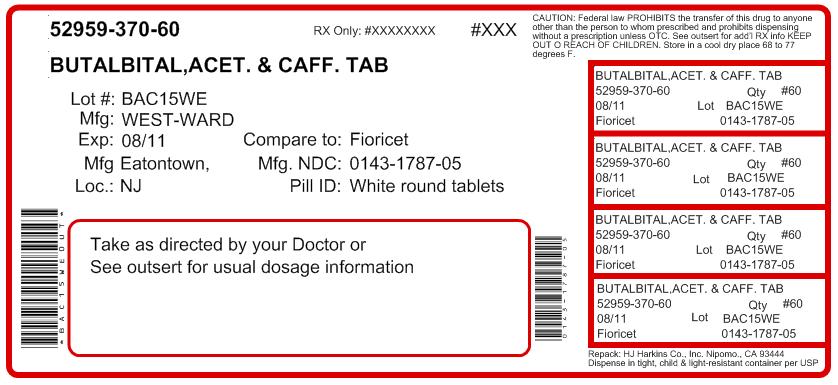 DRUG LABEL: Butalbital, Aspirin and Caffeine
NDC: 52959-370 | Form: TABLET
Manufacturer: H.J. Harkins Company
Category: prescription | Type: HUMAN PRESCRIPTION DRUG LABEL
Date: 20120103
DEA Schedule: CIII

ACTIVE INGREDIENTS: BUTALBITAL 50 mg/1 1; ASPIRIN 325 mg/1 1; CAFFEINE 40 mg/1 1
INACTIVE INGREDIENTS: CELLULOSE, MICROCRYSTALLINE; SODIUM STARCH GLYCOLATE TYPE A POTATO; TALC; HYDROGENATED COTTONSEED OIL; STARCH, CORN

Butalbital, Aspirin and Caffeine Tablets, USP

Butalbital, Aspirin and Caffeine Tablets, USP CIII

Rx Only

Rev. 01/09

DESCRIPTION:

Each Butalbital, Aspirin, and Caffeine tablet for oral administration contains:

Butalbital, USP 50 mg

Aspirin, USP 325 mg

Caffeine, USP 40 mg

Butalbital, 5-allyl-5-isobutyl-barbituric acid, a white odorless crystalline powder; is a short-to intermediate-acting barbiturate. Its structural formula is as follows:

Aspirin, salicylic acid acetate, is a non-opiate analgesic, anti-inflammatory and antipyretic agent. It occurs as a white, crystalline tabular or needle-like powder and is odorless or has a faint odor. Its structural formula is as follows:

Caffeine, 1,3,7-trimethylxanthine, is a central nervous system stimulant which occurs as a white powder or white glistening needles. It also has a bitter taste. Its structural formula is as follows:

Inactive Ingredients: Hydrogenated Vegetable Oil, Microcrystalline Cellulose, Sodium Starch Glycolate, Starch 1500 and Talc.

CLINICAL PHARMACOLOGY

Pharmacologically, butalbital, aspirin, and caffeine combines the analgesic properties of aspirin with the anxiolytic and muscle relaxant properties of butalbital.

The clinical effectiveness of butalbital, aspirin, and caffeine in tension headache has been established in double-blind, placebo-controlled, multi-clinic trials. A factorial design study compared butalbital, aspirin, and caffeine with each of its major components. This study demonstrated that each component contributes to the efficacy of butalbital, aspirin, and caffeine in the treatment of the target symptoms of tension headache (headache pain, psychic tension, and muscle contraction in the head, neck, and shoulder region). For each symptom and the symptom complex as a whole, butalbital, aspirin, and caffeine was shown to have significantly superior clinical effects to either component alone.

Pharmacokinetics:

The behavior of the individual components is described below.

Aspirin:

The systemic availability of aspirin after an oral dose is highly dependent on the dosage form, the presence of food, the gastric emptying time, gastric pH, antacids, buffering agents, and particle size. These factors affect not necessarily the extent of absorption of total salicylates but more the stability of aspirin prior to absorption.

During the absorption process and after absorption, aspirin mainly hydrolyzed to salicylic acid and distributed to all body tissues and fluids, including fetal tissues, breast milk, and the central nervous system (CNS). Highest concentrations are found in plasma, liver, renal cortex, heart, and lung. In plasma, about 50%-80% of the salicylic acid and its metabolites are loosely bound to plasma proteins.

The clearance of total salicylates is subject to saturable kinetics; however, first-order elimination kinetics are still a good approximation for doses up to 650 mg. The plasma half-life for aspirin is about 12 minutes and for salicylic acid and/or total salicylates is about 3.0 hours.

The elimination of therapeutic doses is through the kidneys either as salicylic acid or other biotransformation products. The renal clearance is greatly augmented by an alkaline urine as is produced by concurrent administration of sodium bicarbonate or potassium citrate.

The biotransformation of aspirin occurs primarily in the hepatocytes. The major metabolites are salicyluric acid (75%), the phenolic and acyl glucuronides of salicylate (15%), and gentisic and gentisuric acid (1%). The bioavailability of the aspirin component butalbital, aspirin, and caffeine is equivalent to that of a solution except for a slower rate of absorption. A peak concentration of 8.80 mcg/mL was obtained at 40 minutes after a 650 mg dose. (see OVERDOSAGE for toxicity information).

Butalbital:

Butalbital is well absorbed from the gastrointestinal tract and is expected to distribute to most of the tissues in the body. Barbiturates, in general, may appear in breast milk and readily cross the placental barrier. They are bound to plasma and tissue proteins to a varying degree and binding increases directly as a function of lipid solubility.

Elimination of butalbital is primarily via the kidney (59%-88% of the dose) as unchanged drug or metabolites. The plasma half-life is about 35 hours. Urinary excretion products included parent drug (about 3.6% of the dose), 5-isobutyl-5-(2,3-dihydroxypropyl) barbituric acid (about 24% of the dose), 5-allyl-5(3-hydroxy-2-methyl-1-propyl) barbituric acid (about 4.8% of the dose), products with the barbituric acid ring hydrolyzed with excretion of urea (about 14% of the dose), as well as unidentified materials. Of the material excreted in the urine, 32% was conjugated.

The bioavailability of the butalbital component of butalbital, aspirin, and caffeine is equivalent to that of a solution except for a decrease in the rate of absorption. A peak concentration of 2020 ng/mL is obtained at about 1.5 hours after a 100 mg dose.

The in vitro plasma protein binding of butalbital is 45% over the concentration range of 0.5 to 20 mcg/mL. This falls within the range of plasma protein binding (20% to 45%) reported with other barbiturates such as phenobarbital, pentobarbital, and secobarbital sodium. The plasma-to-blood concentration ratio was almost unity indicating that there is no preferential distribution of butalbital into either plasma or blood cells. (see OVERDOSAGE for toxicity information).

Caffeine:

Like most xanthines, caffeine is rapidly absorbed and distributed in all body tissues and fluids, including the CNS, fetal tissues, and breast milk.

Caffeine is cleared rapidly through metabolism and excretion in the urine. The plasma half-life is about 3.0 hours. Hepatic biotransformation prior to excretion results in about equal amounts of 1-methyl-xanthine and 1-methyluric acid. Of the 70% of the dose that has been recovered in the urine, only 3% was unchanged drug.

The bioavailability of the caffeine component for butalbital, aspirin, and caffeine is equivalent to that of a solution except for a slightly longer time to peak. A peak concentration of 1660 ng/mL was obtained in less than an hour for an 80 mg dose (see OVERDOSAGE for toxicity information).

INDICATIONS AND USAGE

Butalbital, aspirin, and caffeine tablets are indicated for the relief of the symptom complex of tension (or muscle contraction) headache.

Evidence supporting the efficacy and safety of butalbital, aspirin, and caffeine in the treatment of multiple recurrent headaches is unavailable. Caution in this regard is required because butalbital is habit-forming and potentially abusable.

CONTRAINDICATIONS

Hypersensitivity to aspirin, caffeine, or barbiturates. Patients with porphyria.

WARNINGS

Drug Dependency:

Prolonged use of barbiturates can produce drug dependence, characterized by psychic dependence, and less frequently, physical dependence and tolerance. The abuse liability of butalbital, aspirin, and caffeine is similar to that of other barbiturate-containing drug combinations. Caution should be exercised when prescribing medication for patients with a known propensity for taking excessive quantities of drugs, which is not uncommon in patients with chronic tension headache.

Use in Ambulatory Patients:

Butalbital, aspirin, and caffeine may impair the mental and/or physical abilities required for the performance of potentially hazardous tasks, such as driving a car or operating machinery. The patient should be cautioned accordingly. Central Nervous System depressant effects of butalbital may be additive with those of other CNS depressants. Concurrent use with other sedative-hypnotics or alcohol should be avoided. When such combined therapy is necessary, the dose of one or more agents may need to be reduced.

Use in Pregnancy:

Adequate studies have not been performed in animals to determine whether this drug affects fertility in males or females, has teratogenic potential, or has other adverse effects on the fetus. While there are no well-controlled studies in pregnant women, over twenty years of marketing and clinical experience does not include any positive evidence of adverse effects on the fetus. Although there is no clearly defined risk, such experience cannot exclude the possibility of infrequent or subtle damage to the human fetus. Butalbital, aspirin, and caffeine should be used in pregnant women only when clearly needed.

Nursing Mothers:

The effects of butalbital, aspirin, and caffeine on infants of nursing mothers are not known. Salicylates and barbiturates are excreted in the breast milk of nursing mothers. The serum levels in infants are believed to be insignificant with therapeutic doses.

PRECAUTIONS

Salicylates should be used with extreme caution in the presence of peptic ulcer or coagulation abnormalities.

Pediatric Use:

Safety and effectiveness in pediatric patients below the age of 12 have not been established.

ADVERSE REACTIONS

The most frequent adverse reactions are drowsiness and dizziness. Less frequent adverse reactions are lightheadedness and gastrointestinal disturbances including nausea, vomiting, and flatulence. A single incidence of bone marrow suppression has been reported with the use of butalbital, aspirin, and caffeine. Several cases of dermatological reactions including toxic epidermal necrolysis and erythema multiforme have been reported.

OVERDOSAGE

The toxic effects of acute overdosage of butalbital, aspirin, and caffeine are attributable mainly to its barbiturate component, and, to a lesser extent, aspirin. Because toxic effects of caffeine occur in very high dosages only, the possibility of significant caffeine toxicity from butalbital, aspirin, and caffeine overdosage is unlikely. Symptoms attributable to acute barbiturate poisoning include drowsiness, confusion, and coma; respiratory depression; hypotension; shock. Symptoms attributable to acute aspirin poisoning include hyperpnea; acid-base disturbances with development of metabolic acidosis; vomiting and abdominal pain; tinnitus; hyperthermia; hypoprothrombinemia; restlessness; delirium; convulsions. Acute caffeine poisoning may cause insomnia, restlessness, tremor, and delirium; tachycardia and extrasystoles. Treatment consists primarily of management of barbiturate intoxication and the correction of the acid-base imbalance due to salicylism. Vomiting should be induced mechanically or with emetics in the conscious patient. Gastric lavage may be used if the pharyngeal and laryngeal reflexes are present and if less than 4 hours have elapsed since ingestion. A cuffed endotracheal tube should be inserted before gastric lavage of the unconscious patient and when necessary to provide assisted respiration. Diuresis, alkalinization of the urine, and correction of electrolyte disturbances should be accomplished through administration of intravenous fluids such as 1% sodium bicarbonate in 5% dextrose in water. Meticulous attention should be given to maintaining adequate pulmonary ventilation. Correction of hypotension may require the administration of levartherenol bitartrate or phenylephrine hydrochloride by intravenous infusion . In severe cases of intoxication, peritoneal dialysis, hemodialysis, or exchange transfusion may be lifesaving. Hypoprothrombinemia should be treated with Vitamin K, intravenously.

DOSAGE AND ADMINISTRATION

One or two tablets every 4 hours. Total daily dose should not exceed 6 tablets.

HOW SUPPLIED:

Butalbital, Aspirin, and Caffeine Tablets, USP 50 mg/325 mg/40 mg are White, Round, Unscored Compressed Tablets Imprinted “West-ward 785”.

Bottles of 30 tablets
Bottles of 50 tablets
Bottles of 100 tablets
Bottles of 500 tablets
Bottles of 1000 tablets
Unit Dose Boxes of 100 tablets

Store at 20-25oC (68-77oF) [See USP Controlled Room Temperature]. Protect from light and moisture.

Dispense in a tight, light-resistant container as defined in the USP using a child-resistant closure.

Manufactured By:
West-ward Pharmaceutical Corp
Eatontown, NJ 07724

Revised. January 2009